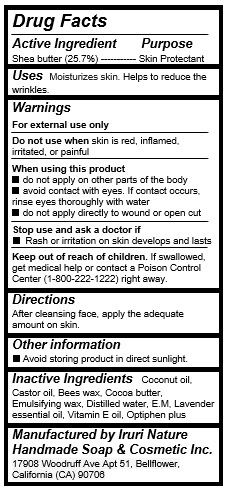 DRUG LABEL: EM Shea Butter Cream
NDC: 71547-102 | Form: CREAM
Manufacturer: Iruri Nature Handmade Soap & Cosmetic Inc
Category: otc | Type: HUMAN OTC DRUG LABEL
Date: 20170713

ACTIVE INGREDIENTS: SHEA BUTTER 5.14 g/20 mL
INACTIVE INGREDIENTS: YELLOW WAX; COCOA BUTTER; .ALPHA.-TOCOPHEROL; COCONUT OIL; CASTOR OIL; WATER; LAVENDER OIL

EM Shea Butter Cream

Active Ingredients

Shea Butter (25.7%)

Purpose

Skin protectant

Keep out of reach of children

If swallowed, get medical help or contact a Poison Control Center (1-800-222-1222) right away.

Uses

Moisturizes skin.

Warnings

For external use only

Do not use when skin is red, inflamed, irritated, or painful

When using this product

- do not apply on other parts of the body
- avoid contact with eyes. If contact occurs, rinse eyes thoroughly with water
- do not apply directly to wound or open cut

Stop use and ask a doctor if

- Rash or irritation on skin develops and lasts

Directions

After cleansing face, apply the adequate amount on skin.

Inactive ingredients

Coconut oil, Castor oil, Bees wax, Cocoa butter, Emulsifying wax, Distilled water, E.M, Lavender essential oil, Vitamin E oil, Optiphen plus